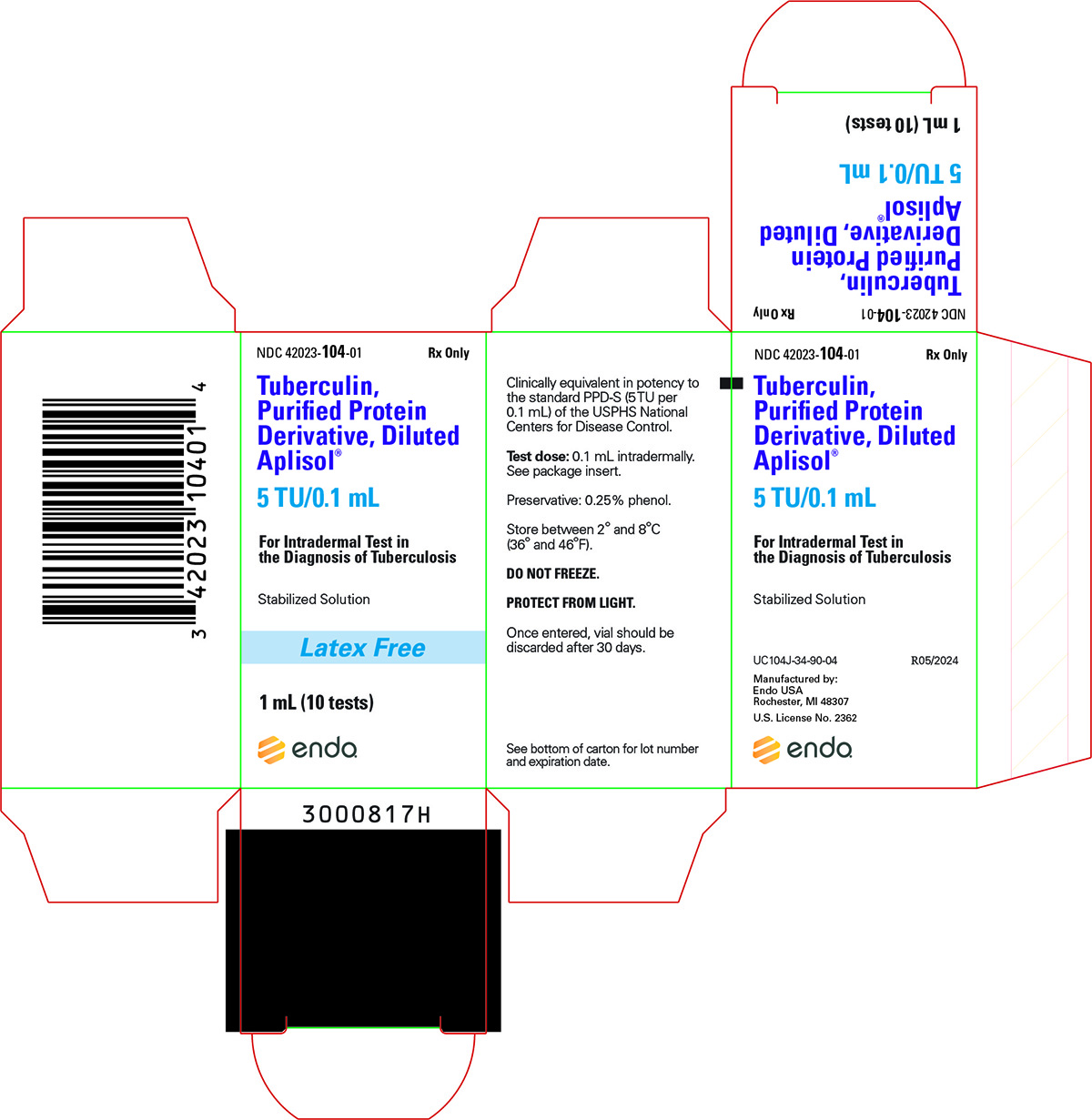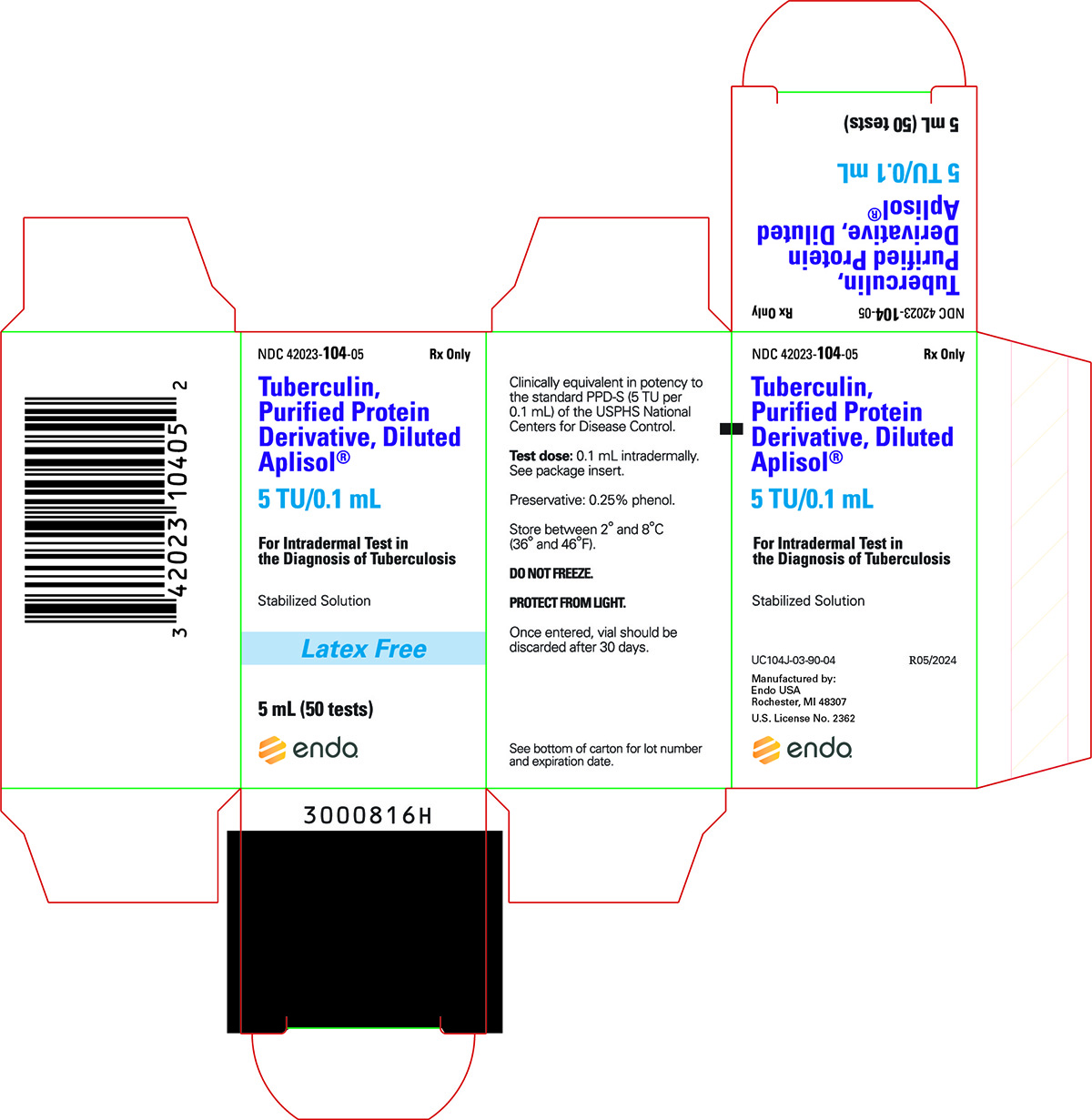 DRUG LABEL: Aplisol
NDC: 42023-104 | Form: INJECTION
Manufacturer: ENDO USA, Inc.
Category: prescription | Type: HUMAN PRESCRIPTION DRUG LABEL
Date: 20240820

ACTIVE INGREDIENTS: TUBERCULIN PURIFIED PROTEIN DERIVATIVE 5 [iU]/0.1 mL
INACTIVE INGREDIENTS: POLYSORBATE 80; PHENOL

APLISOL®
(Tuberculin Purified Protein Derivative, Diluted [Stabilized Solution])

Diagnostic Antigen For Intradermal Injection Only

DESCRIPTION

Aplisol (tuberculin PPD, diluted) is a sterile aqueous solution of a purified protein fraction for intradermal administration as an aid in the diagnosis of tuberculosis. The solution is stabilized with polysorbate (Tween) 80, buffered with potassium and sodium phosphates and contains approximately 0.25% phenol as a preservative.

This product is ready for immediate use without further dilution.

The purified protein fraction is isolated from culture media filtrates of a human strain of Mycobacterium tuberculosis by the method of F.B. Seibert.^1,2 Tuberculin PPD, diluted, is prepared from Tuberculin PPD which is clinically bioequivalent in potency to the standard PPD-S* (5 TU** per 0.1mL) of the U.S. Public Health Service, National Centers for Disease Control.

The potency of each lot of tuberculin PPD, diluted is determined in sensitized guinea pigs.

CLINICAL PHARMACOLOGY

In the United States, the prevalence of Mycobacterium tuberculosis infection and active disease varies for different segments of the population; however, the risk for M. tuberculosis infection in the overall population is low. Tuberculosis (TB) case rates declined steadily for decades in the United States. However, in 1985 the TB case rate stabilized and subsequently increased through 1992, accompanied by a 14% increase in the TB mortality rate in 1988. This has been attributed to several complex social and medical factors, including the human immunodeficiency virus (HIV) epidemic, the occurrence of TB in foreign-born persons from countries that have a high prevalence of TB, the emergence of drug-resistant strains of TB, and the transmission of M. tuberculosis in congregate settings (e.g., health-care facilities, correctional facilities, drug-treatment centers, and homeless shelters). Because the overall risk of acquiring M. tuberculosis is low for the total U.S. population, the primary strategy for preventing and controlling TB in the United States is to minimize the risk of transmission by the early identification and treatment of patients who have active infectious TB, finding and screening persons who have been in contact with active infectious TB patients and screening high risk populations.

Tuberculin PPD is indicated as an aid in the detection of infection with Mycobacterium tuberculosis.^3,4 After a person becomes infected with mycobacteria, T lymphocytes proliferate and become sensitized. These sensitized T cells enter the bloodstream and circulate for months or years. This sensitization process occurs principally in the regional lymph nodes and may take 2–10 weeks to develop following infection. Once acquired, tuberculin sensitivity tends to persist, although it often wanes with time and advancing age. The injection of tuberculin into the skin stimulates the lymphocytes and activates the series of events leading to a delayed-type hypersensitivity (DTH) response. This response is called "delayed" because the reaction becomes evident hours after injection. Dermal reactivity involves vasodilation, edema, and the infiltration of lymphocytes, basophils, monocytes, and neutrophils into the site of antigen injection. Antigen-specific T lymphocytes proliferate and release lymphokines, which mediate the accumulation of other cells at the site. The area of induration reflects DTH activity.^5 In most tuberculin-sensitive individuals, the delayed hypersensitivity reaction is evident 5–6 hours after administration of a tuberculin skin test and is maximal 48–72 hours. In geriatric patients or in patients receiving a tuberculin skin test for the first time, the reaction may develop more slowly and may not be maximal until after 72 hours.^6,7 Because their immune systems are immature, many neonates and infants <6 weeks of age, who are infected with M. tuberculosis, do not react at all to tuberculin tests.^5

Immediate erythematous or other hypersensitivity reactions to tuberculin or the constituents of the diluent may occur at the injection site.

A possible decrease in responsiveness to skin testing may occur in the presence of infections, viral infections (measles, mumps, chickenpox, HIV), live virus vaccinations (measles, mumps, rubella, oral polio, varicella, yellow fever), bacterial infections (typhoid fever, brucellosis, typhus, leprosy, pertussis, overwhelming tuberculosis, tuberculous pleurisy), fungal infections (South American blastomycosis), drugs (corticosteroids and other immunosuppressive agents), metabolic derangements (chronic renal failure), low protein states (severe protein depletion, afibrinogenemia), age (newborns, elderly patients with waned sensitivity), stress (surgery, burns, mental illness, graft-versus-host reactions), diseases affecting lymphoid organs (Hodgkin's disease, lymphoma, chronic leukemia, sarcoidosis) and malignancy (see WARNINGS).

Tuberculin skin-test results are also less reliable as CD4 counts decline in HIV infected individuals.^3

The 5TU dose of Tuberculin PPD intradermally (Mantoux) is indicated as an aid in the detection of infection with Mycobacterium tuberculosis. Reactions to the Mantoux test are interpreted on the basis of a quantitative measurement of the response to a specific dose (5 TU PPD-S or equivalent) of Tuberculin PPD.^7

To determine that the Tuberculin PPD is clinically bioequivalent in potency to standard 5TU PPD-S*, 3 dose-response studies were conducted in the following populations (1) persons with a history of bacteriologically confirmed TB; (2) healthy volunteers; and (3) volunteers with active or previously active nontuberculosis mycobacterial lung disease.

INDICATIONS AND USAGE

Tuberculin PPD is indicated as an aid in the detection of infection with Mycobacterium tuberculosis. The standard tuberculin test employs the intradermal (Mantoux) test using a 5 TU dose of tuberculin PPD.^7 The 0.1 mL test dose of Aplisol (tuberculin PPD, diluted) is equivalent to the 5 TU dose which has been clinically utilized and standardized with PPD-S. Tuberculin skin testing is not contraindicated for persons who have been vaccinated with BCG and the skin-test results of such persons are used to support or exclude the diagnosis of M. tuberculosis infections.^4 HIV infection is a strong risk factor for the development of TB disease in persons having TB infection. All HIV-infected persons should receive a PPD-tuberculin skin test.^3

CONTRAINDICATIONS

Aplisol is contraindicated in patients with known hypersensitivity or allergy to Aplisol or any of its components. Aplisol should not be administered to persons who have previously experienced a severe reaction (e.g., vesiculation, ulceration, or necrosis) because of the severity of reactions that may occur at the test site.

WARNINGS

Aplisol should not be administered to persons who previously experienced a severe reaction (e.g., vesiculation, ulceration, or necrosis) because of the severity of reactions that may occur at the test site (see CONTRAINDICATIONS).

Not all infected persons will have a delayed hypersensitivity reaction to a tuberculin test. A number of factors have been reported to cause a decreased ability to respond to the tuberculin test, such as the presence of infections, viral infections (measles, mumps, chickenpox, HIV), live virus vaccinations (measles, mumps, rubella and other live vaccines), bacterial infections (typhoid fever, brucellosis, typhus, leprosy, pertussis, overwhelming tuberculosis, tuberculous pleurisy), fungal infections (South American blastomycosis), drugs (corticosteroids and other immunosuppressive agents), metabolic derangements (chronic renal failure), low protein states (severe protein depletion, afibrinogenemia), age (newborns, elderly patients with waned sensitivity), stress (surgery, burns, mental illness, graft-versus-host reactions), diseases affecting lymphoid organs (Hodgkin's disease, lymphoma, chronic leukemia, sarcoidosis), and malignancy.^7,8,9

Any condition that impairs or attenuates cell mediated immunity potentially can cause a false negative reaction, including aging.^10,11

Tuberculin skin test results are less reliable in HIV-infected individuals as CD4 counts decline (see CLINICAL PHARMACOLOGY).^3

Avoid injecting tuberculin subcutaneously. If this occurs, no local reaction develops, but a general febrile reaction and/or acute inflammation around old tuberculous lesions may occur in highly sensitive individuals.

PRECAUTIONS

General

The predictive value of the tuberculin skin test depends on the prevalence of infection with M. tuberculosis and the relative prevalence of cross-reactions with nontuberculous mycobacteria.^9,12

A separate, sterile, single-use disposable syringe and needle should be used for each individual patient to prevent possible transmission of serum hepatitis virus and other infectious agents from one person to another. Special care should be taken to ensure that the product is injected intradermally and not into a blood vessel.

Before administration of Aplisol, a review of the patient's history with respect to possible immediate-type hypersensitivity to the product, determination of previous use of Aplisol and the presence of any contraindication to the test should be made (see CONTRAINDICATIONS).

As with any biological product, epinephrine should be immediately available in case an anaphylactoid or acute hypersensitivity reaction occurs.

Failure to store and handle Aplisol as recommended may result in a loss of potency and inaccurate test results.^8,13

Reactivity to the test may be depressed or suppressed for as long as 5–6 weeks in individuals following immunization with certain live viral vaccines, viral infections or discontinuation of corticosteroids or immunosuppressive agents.^8,9

Information to Patients

Patients should be instructed to report adverse events such as vesiculation, ulceration or necrosis which may occur at the test site in highly sensitive individuals. Patients should be informed that pain, pruritus and discomfort may occur at injection site.

Patients should be informed of the need to return to their physician or health care provider for the reading of the test and of the need to keep and maintain a personal immunization record.

Drug Interactions

In patients who are receiving corticosteroids or immunosuppressive agents, reactivity to the test may be depressed or suppressed. This reduced reactivity may be present for as long as 5–6 weeks after discontinuation of therapy (see PRECAUTIONS – General).^9

The reactivity to PPD may be temporarily depressed by certain live virus vaccines (measles, mumps, rubella, oral polio, yellow fever, and varicella). Therefore, if a tuberculin test is to be performed, it should be administered either before the live vaccine or given simultaneously, but at a separate site than the live vaccine, or testing should be postponed for 4–6 weeks.^9

Carcinogenesis, Mutagenesis, Impairment of Fertility

No long term studies have been conducted in animals or in humans to evaluate carcinogenic or mutagenic potential or effects on fertility with Aplisol.

Pregnancy

Teratogenic effects:

Pregnancy Category C

Animal reproduction studies have not been conducted with Aplisol. It is also not known whether Aplisol can cause fetal harm when administered to a pregnant woman or can affect the reproduction capacity. Aplisol should be given to a pregnant woman only if clearly needed. However, the risk of unrecognized tuberculosis and the postpartum contact between a mother with active disease and an infant leaves the infant in grave danger of tuberculosis and complications such as tuberculous meningitis. Although there have not been any reported adverse effects upon the fetus recognized as being due to tuberculosis skin testing, the prescribing physician will want to consider if the potential benefits outweigh the possible risks for performing the tuberculin test on a pregnant woman or a woman of childbearing age, particularly in certain high risk populations.

Tuberculin skin testing is considered valid and safe throughout pregnancy.^3

Geriatric Use

Once acquired, tuberculin sensitivity tends to persist, although it often wanes with time and advancing age. In geriatric patients or in patients receiving a tuberculin skin test for the first time, the reaction may develop more slowly and may not be maximal until after 72 hours.^6,7 (see CLINICAL PHARMACOLOGY). Not all infected persons will have a delayed hypersensitivity reaction to a tuberculin test. A number of factors have been reported to cause a decreased ability to respond to the tuberculin test, such as elderly patients with waned sensitivity.^7 Any condition that impairs or attenuates cell mediated immunity potentially can cause a false negative reaction, including aging^10,11 (see WARNINGS). An induration of >10 mm is classified as positive in all persons who do not meet any of the criteria listed under an induration of >5 mm, but who belong to one or more of the following groups at high risk for TB, including residents and employees of high risk congregate settings, such as nursing homes and other long-term facilities for the elderly.

The negative tuberculin skin test should never be used to exclude the possibility of active tuberculosis among person for whom the diagnosis is being considered (symptoms compatible with tuberculosis) (see DOSAGE AND ADMINISTRATION-Interpretation of Tuberculin Reaction).

Pediatric Use

Because their immune systems are immature, many neonates and infants <6 weeks of age, who are infected with M. tuberculosis, may not have a delayed hypersensitivity reaction to a tuberculin test (see WARNINGS). Older infants and children develop tuberculin sensitivity 3-6 weeks, and up to 3 months, after initial infection.^5,20 Infants and children who have been exposed to persons with active tuberculosis should be considered positive when reaction to the tuberculin skin test measures ≥ 5 mm. Those children younger than 4 years of age who are exposed to persons at increased risk to acquire tuberculosis are considered positive when reaction measures ≥10 mm. Children with minimal risk exposure to tuberculosis would be considered positive when reaction measures ≥15 mm. ^5,20 Other criteria for positive tuberculin reactions that are applicable to both pediatric and adult patients are provided in DOSAGE AND ADMINISTRATION, Interpretation of Tuberculin Reaction.

ADVERSE REACTIONS

In highly sensitive individuals, strongly positive reactions including vesiculation, ulceration or necrosis may occur at the test site. Cold packs or topical steroid preparations may be employed for symptomatic relief of the associated pain, pruritus and discomfort.

Strongly positive test reactions may result in scarring at the test site.

Immediate erythematous or other reactions may occur at the injection site.

Local hypersensitivity reactions may occur at the injection site including erythema, pruritus, edema, urticaria and rash.

Systemic allergic reactions including anaphylaxis/anaphylactoid reactions have been reported to occur in association with the use of Aplisol. The reactions, including anaphylaxis, generally occurred within 24 hours of exposure and manifestations included rash, urticaria, edema/angioedema and pruritus.

To report SUSPECTED ADVERSE REACTIONS, contact Endo at 1-800-828-9393 or FDA at 1-800-FDA-1088 or www.fda.gov/medwatch.

DOSAGE AND ADMINISTRATION

Aplisol vials should be inspected visually for both particulate matter and discoloration prior to administration and discarded if either is seen. Vials in use for more than 30 days should be discarded.

The 0.1 mL dose of Aplisol (tuberculin PPD, diluted) is equivalent to the 5 tuberculin units (TU) dose of Tuberculin PPD, which is the standard strength used for intradermal Mantoux testing.

Standard Method (Mantoux Test)

The Mantoux test is performed by intradermally injecting, on the volar aspect of the forearm, with a syringe and needle, exactly 0.1 mL of Aplisol. The result is read 48 to 72 hours later and palpable induration only is considered in interpreting the test. Induration is a hard, raised area with clearly defined margins at and around the injection site (see Interpretation of Tuberculin Reaction). Erythema may develop at the injection site but has no diagnostic value.

The standard test is performed as follows:

1. The site of the test is usually the volar or dorsal surface of the forearm about 4" below the elbow. Other skin sites may be used, but the volar surface of the forearm is preferred. The use of a skin area free of lesions and away from any veins is recommended.^7
2. The skin at the injection site is cleansed with 70% alcohol and allowed to dry.
3. The test material is administered with a tuberculin syringe (0.5 or 1.0 mL) fitted with a short (1/4 to 1/2") 27 gauge needle.
4. A separate, sterile, single-use disposable syringe and needle should be used for each individual patient.
5. The diaphragm of the vial-stopper should be wiped with 70% alcohol.
6. The needle is inserted through the stopper diaphragm of the inverted vial. Exactly 0.1 mL is filled into the syringe with care being taken to exclude air bubbles and to maintain the lumen of the needle filled.
7. The point of the needle is inserted into the most superficial layers of the skin with the needle bevel pointed upward. As the Tuberculin solution is injected, a pale bleb 6 to 10 mm in size (1/3") will rise over the point of the needle. This is quickly absorbed and no dressing is required.
8. There may be a drop of blood when the needle is withdrawn. This is normal. Use a gauze pad and gently dab to remove the blood. Do not press down as this may squeeze out the tuberculin thereby disrupting the test.

In the event the injection is delivered subcutaneously (i.e., no bleb will form), or if a significant part of the dose leaks from the injection site, the test should be repeated immediately at another site at least 5 cm (2") removed from the initial injection site.

Interpretation of Tuberculin Reaction

Readings of Mantoux reactions should be made by a trained health professional during the period from 48 to 72 hours after the injection. Induration only should be considered in interpreting the test. The diameter of induration should be measured transversely to the long axis of the forearm and recorded in millimeters. Erythema has no diagnostic value and should be disregarded. The presence and size of necrosis and edema if present should be recorded although not used in the interpretation of the test. In the absence of induration, an area of erythema greater than 10 mm in diameter may indicate the injection was made too deeply and retesting is indicated. Find the margins of the induration by drawing the index or middle finger lightly across the reaction. The tip of a ballpoint pen pushed at a 45° angle toward the site of injection will also stop at the edges of induration.

The diameter of induration should be measured (preferable with a caliper) transversely to the long axis of the forearm and recorded in millimeters.

Erythema has no diagnostic value and should be disregarded. The absence of induration should be recorded as "0 mm" not "negative".

Reactions should be interpreted as follows (Please refer to most recent guidelines):

Based on current guidelines,^(3,7,14, 19) interpretation of reactions is as follows:

Positive reactions:

Reaction ≥ 5 mm of Induration | Reaction ≥ 10 mm of Induration | Reaction ≥ 15 mm of Induration
Human immunodeficiency virus (HIV)-positive persons | Recent immigrants (i.e., within the last 5 yr) from high prevalence countries | Persons with no risk factors for TB
Recent contacts of tuberculosis (TB) case patients | Injection drug users
Fibrotic changes on chest radiograph consistent with prior TB | Residents and employees [For persons who are otherwise at low risk and are tested at the start of employment, a reaction of ≥ 15 mm induration is considered positive.] of the following high-risk congregate settings: prisons and jails, nursing homes and other long-term facilities for the elderly, hospitals and other health care facilities, residential facilities for patients with acquired immunodeficiency syndrome (AIDS), and homeless shelters
Patients with organ transplants and other immunosuppressed patients (receiving the equivalent of ≥ 15 mg/d of prednisone for 1 mo or more) [Risk of TB in patients treated with corticosteroids increases with higher dose and longer duration. ^19] | Mycobacteriology laboratory personnel
 | Persons with the following clinical conditions that place them at high risk: silicosis, diabetes mellitus, chronic renal failure, some hematological disorders (e.g., leukemias and lymphomas), other specific malignancies (e.g., carcinoma of the head or neck and lung), weight loss of ≥ 10% of ideal body weight, gastrectomy, and jejunoileal bypass
 | Children younger than 4 yr of age or infants, children, and adolescents exposed to adults at high-risk

Skin test conversions

- For persons with negative skin test reactions who undergo repeat skin testing (e.g., health care workers), an increase in reaction size ≥ 10 mm within a period of 2 years should be considered a skin test conversion indicative of recent infection with M. tuberculosis. ^19
- In some individuals who have been infected with nontuberculous mycobacteria or have undergone BCG vaccination, the skin test may show some degree of induration. For these individuals, a conversion to "positive" is defined as an increase in induration by 10 mm on subsequent tests. ^7

Healthcare facilities and other high-risk settings

- For health care workers and employees in other high-risk settings with no other risk factors for TB, a cut-off of 15 mm of induration (rather than 10 mm) on the tuberculin skin test should be used to define a positive baseline test at the time of initial employment.
- An increase of ≥10 mm in reaction size is generally accepted as a positive test result on subsequent testing unless the worker is a contact of a TB case or has HIV infection or is otherwise immunocompromised, in which case a result of ≥5 mm is considered positive. ^21

Negative Reaction

A negative reaction is an induration of less than 15 mm in persons with no risk factors for TB. This indicates a lack of hypersensitivity to tuberculoprotein and tuberculous infection is highly unlikely.^7

It should be noted that reactivity to tuberculin may be depressed or suppressed for as long as 5–6 weeks by viral infections, live virus vaccines (i.e., measles, smallpox, polio, rubella and mumps), or after discontinuation of therapy with corticosteroids or immunosuppressive agents. Malnutrition may also have a similar effect (see WARNINGS). When of diagnostic importance, a negative test should be accepted as proof that hypersensitivity is absent only after normal reactivity to non-specific irritants has been demonstrated. A primary injection of tuberculin may possibly have a boosting effect on subsequent tuberculin reactions. A pediatric patient who is known to have been exposed to a person with tuberculosis must not be adjudged free of infection until that patient has a negative tuberculin reaction at least ten weeks after contact with tuberculous person has ceased.^17 Annual testing is generally recommended for pediatric patients in high risk populations, such as persons from countries with a high prevalence of tuberculosis and low-income groups.^18

A positive tuberculin reaction does not necessarily signify the presence of active disease. Further diagnostic procedures (e.g., chest radiograph, sputum smear and/or culture examination) should be carried out before a diagnosis of tuberculosis is made. A small percentage of responders may not have been infected with M. tuberculosis but by some other mycobacterium. The negative tuberculin skin test should never be used to exclude the possibility of active tuberculosis among persons for whom the diagnosis is being considered (symptoms compatible with tuberculosis).

Booster Effect and Two-Step Testing

Infection of an individual with tubercle bacilli or other mycobacteria or BCG vaccination results in a delayed hypersensitivity response to tuberculin which is demonstrated by the skin test. The delayed hypersensitivity response may gradually wane over a period of years. If a person receives a tuberculin test at this time, a significant reaction may not be detected. However, the stimulus of the test may boost or increase the size of the reaction to a second test, sometimes causing an apparent conversion or development of sensitivity. This booster effect can be seen on a second test done one week after the initial stimulating test and can persist for a year, and perhaps longer. When routine periodic tuberculin testing of adults is done, initially two-stage testing should be considered to minimize the likelihood of interpreting a boosted reaction as a conversion.^7,15,16

In this testing method, persons who have a negative initial skin test undergo a second tuberculin skin test 1-3 weeks after the first. Both tests should be read and recorded at 48 to 72 hours. Those individuals with a positive reaction on the second test should be considered to be previously infected, and those with a negative reaction on the second test should be considered uninfected. In these uninfected persons, a positive result on any future skin test should be interpreted as a skin test conversion. ^7

HOW SUPPLIED

Tuberculin PPD-Aplisol bioequivalent to 5 US units (TU) PPD-S per test dose (0.1 mL) is available in the following presentations:

NDC 42023-104-01 (Bio. 1525)

1 mL (10 tests) – multiple dose vial

NDC 42023-104-05 (Bio.1607)

5 mL (50 tests) – multiple dose vial

This product is ready for use without further dilution.

Storage

DO NOT FREEZE

This product should be stored between 2° and 8°C (36° and 46°F) and protected from light.

Vials in use more than 30 days should be discarded due to possible oxidation and degradation which may affect potency.

*PPD-S - World Health Organization International PPD-Tuberculin Standard
**U.S. Tuberculin Unit

REFERENCES

1. Seibert, F.B. The isolation and properties of the purified protein derivative of tuberculin: Am Rev Tuberc 1934; 30:713.
2. Seibert, F.B., and Glenn, J.T. Tuberculin purified protein derivative. Preparation and analyses of a large quantity for standard. Am Rev Tuberc 1941; 44:9-25.
3. Centers for Disease Control and Prevention (CDC). Essential components of a tuberculosis prevention and control program; and Screening for tuberculosis and tuberculosis infection in high-risk populations: recommendations of the Advisory Council for the Elimination of Tuberculosis. MMWR 1995;44(RR-11):1-34.
4. Centers for Disease Control and Prevention (CDC). Prevention and control of tuberculosis in correctional facilities: recommendations of the Advisory Council for the Elimination of Tuberculosis. MMWR 1996;45(RR-8):1-27.
5. Huebner RE, Shein MF, Bass JB. The Tuberculin Skin Test. Clin Infect Dis 1993;17:968–75.
6. AHFS Drug Information, 1997, 36:84 pp 1962–1968.
7. American Thoracic Society: Diagnostic standards and classification of tuberculosis in Adults and Children. Am J Respir Crit Care Med 2000 Apr; 161:1376-95.
8. Am Rev Respir Dis 1985;886.
9. Brickman HF et.Al. The Timing of Tuberculin Tests in Relation to Immunization with Live Viral Vaccines. Pediatrics 1975;55:392.
10. Nakayama K, Monma M, Fukushima T, Ohrui T, Sasaki H. Tuberculin responses and risk of pneumonia in immobile elderly patients. Thorax 2000 Oct;55(10):867-9.
11. Fukushima T, Nakayama K, Monma M, Sekizawa K, Sasaki H. Depression of T helper-1 and the tuberculin responses in older bed-bound patients. J Am Geriatri Soc 1999 Feb;47(2):259-260.
12. American Academy of Pediatrics. Tuberculosis. In: Pickering LK, CJ Baker, Long SS, McMillan JA, eds. Red Book: 2006 Report of the Committee on Infectious Diseases, 27th ed. Elk Grove Village, IL: American Academy of Pediatrics 2006: 678-698.
13. Landi S, Held HR. Stability of a dilute solution of tuberculin purified derivative at extreme temperatures. J Biol Stand 1981; 9:195.
14. Centers For Disease Control and Prevention (CDC). Diagnosis of TB Infection and TB Disease, March 21,1996, Doc# 2250102.
15. Sewell, E.M., O'Hare, D., and Kendig, E.L., Jr. The Tuberculin Test. Pediatrics Vol. 54, No. 5, Nov.1974.
16. Centers for Disease Control and Prevention(CDC). Prevention and control of tuberculosis in facilities providing long-term care to the elderly. Recommendations of the Advisory Committee of Elimination of Tuberculosis (ACET): MMWR 1990, 39(RR-10): 7–20.
17. Centers for Disease Control and Prevention(CDC). The use of preventative therapy for tuberculosis infection in the United States, Recommendations of the Advisory Committee of Elimination of Tuberculosis (ACET), MMWR 1990 39(RR-8):9–12.
18. Centers for Disease Control and Prevention(CDC). Screening for tuberculosis and tuberculosis infection in high risk populations. Recommendations of the Advisory Committee of Elimination of Tuberculosis (ACET), MMWR 1990, 39(RR-8): 1-7.
19. Centers for Disease Control and Prevention (CDC). Targeted Tuberculin Testing and Treatment of Latent Tuberculosis Infection. MMWR, 2000. 49(RR-6): 1-51.
20. Pediatrics: Screening for Tuberculosis in Infants and Children, 1994. 93: 131-134.
21. Centers for Disease Control and Prevention (CDC). Controlling Tuberculosis in the United States. MMWR 2005. 54 (RR-12).

Rx only.

Manufactured by:
Endo USA
Rochester, MI 48307

U.S. License No. 2362

© 2024 Endo, Inc. or one of its affiliates.

R05/2024

PRINCIPAL DISPLAY PANEL - 1 mL Carton

NDC 42023-104-01

Rx Only

Tuberculin,
Purified Protein
Derivative, Diluted
Aplisol®

5 TU/0.1 mL

For Intradermal Test in
the Diagnosis of Tuberculosis

Stabilized Solution

Latex Free

1 mL (10 tests)

PRINCIPAL DISPLAY PANEL - 5 mL Carton

NDC 42023-104-05

Rx Only

Tuberculin,
Purified Protein
Derivative, Diluted
Aplisol®

5 TU/0.1 mL

For Intradermal Test in
the Diagnosis of Tuberculosis

Stabilized Solution

Latex Free

5 mL (50 tests)